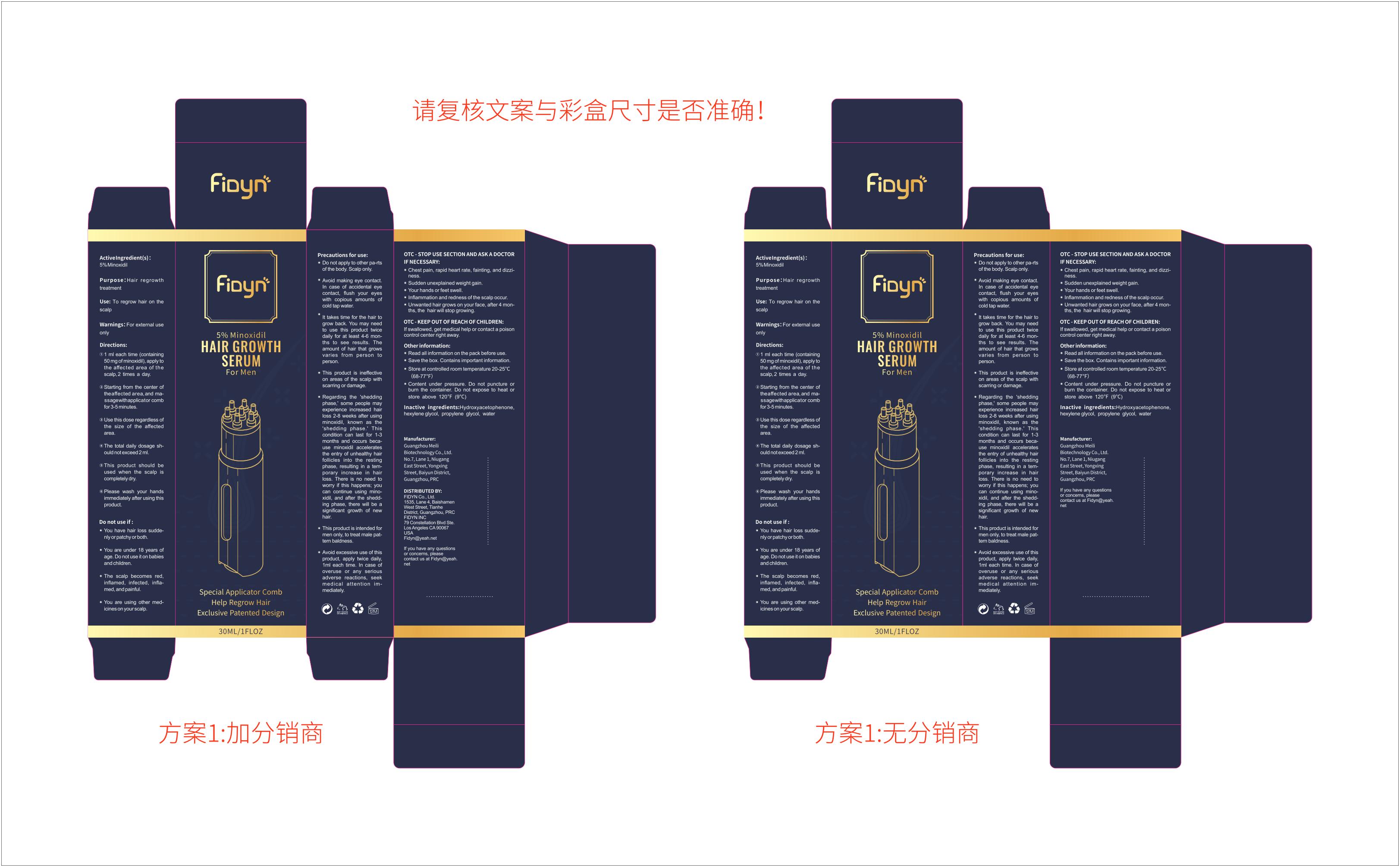 DRUG LABEL: Fidyn 5% Minoxidil HAIR GROWTH SERUM For Men
NDC: 83912-001 | Form: LIQUID
Manufacturer: Fidyn 5% Minoxidil HAIR GROWTH SERUM For Men
Category: otc | Type: HUMAN OTC DRUG LABEL
Date: 20231223

ACTIVE INGREDIENTS: MINOXIDIL 5 g/100 mL
INACTIVE INGREDIENTS: HYDROXYACETOPHENONE; WATER; HEXYLENE GLYCOL; PROPYLENE GLYCOL

83912-001

Active Ingredient

5% Minoxidil

Purpose

Hair regrowth treatment

Use

to regrow hair on the scalp

Warnings

For external use only

Do not use

- If you have hair loss suddenly or patchy or both.
- You are under 18 years of age. Do not use it on babies and children.
- The scalp becomes red, inflamed, infected, inflamed, and painful.
- You are using other medicines on your scalp.

When Using

- Avoid making eye contact. In case of accidental eye contact, flush your eyes with copious amounts of cold tap water.

Stop Use

- Chest pain, rapid heart rate, fainting, and dizziness.
- Sudden unexplained weight gain.
- Your hands or feet swell.
- Inflammation and redness of the scalp occur.
- Unwanted hair grows on your face, after 4 months, the hair will stop growing.

Ask Doctor

- Chest pain, rapid heart rate, fainting, and dizziness.
- Sudden unexplained weight gain.
- Your hands or feet swell.
- Inflammation and redness of the scalp occur.
- Unwanted hair grows on your face, after 4 months, the hair will stop growing.

Keep Oot Of Reach Of Children

‘If swallowed, get medical help or contact a poison control center right away.

Directions

- 1 ml each time (containing 50 mg of minoxidil), apply to the affected area of the scalp, 2 times a day.
- Starting from the center of the affected area, and massage with fingertips for 3-5 minutes.
- Use this dose regardless of the size of the affected area.
- The total daily dosage should not exceed 2 ml.
- This product should be used when the scalp is completely dry.
- Please wash your hands immediately after using this product.

Other information

- Read all information on the pack before use.
- Save the box. Contains important information.
- Store at controlled room temperature 20-25℃（68-77℉）
- Content under pressure. Do not puncture or burn the container. Do not expose to heat or store above 120℉(9℃)

Inactive ingredients

Propylene Glycol, Water

Questions

If you have any questions or concerns, please contact us at Fidyn@yeah.net